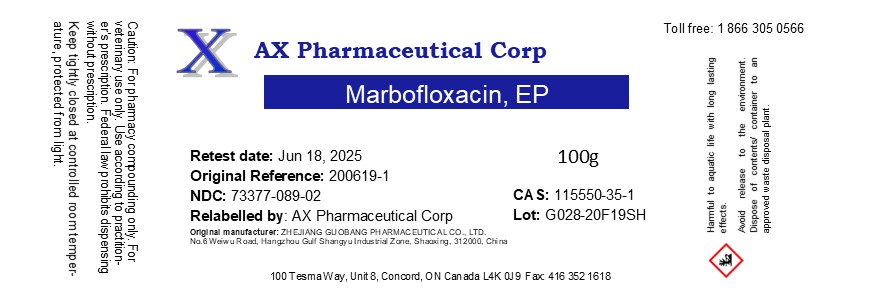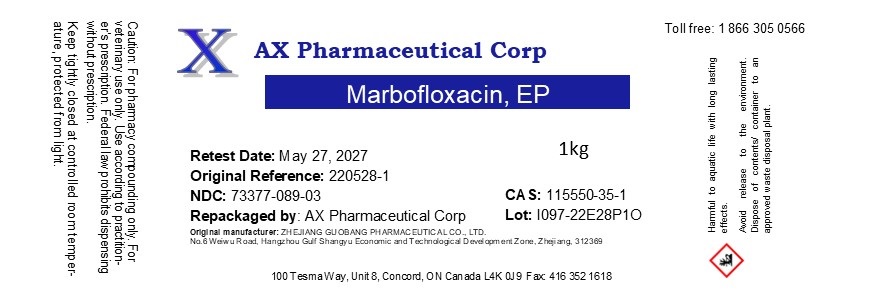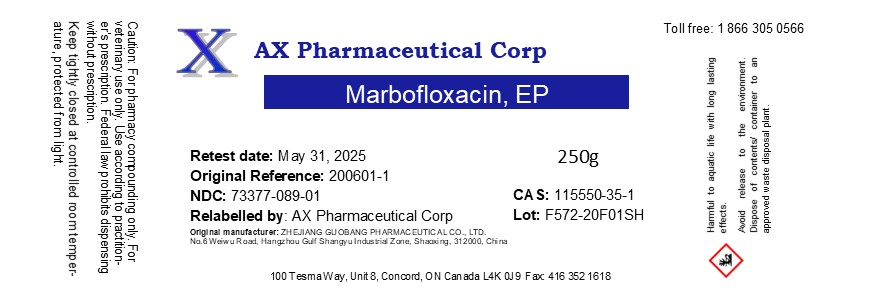 DRUG LABEL: Marbofloxacin
NDC: 73377-089 | Form: POWDER
Manufacturer: AX Pharmaceutical Corp
Category: other | Type: BULK INGREDIENT - ANIMAL DRUG
Date: 20260119

ACTIVE INGREDIENTS: MARBOFLOXACIN 1 g/1 g

Marbofloxacin